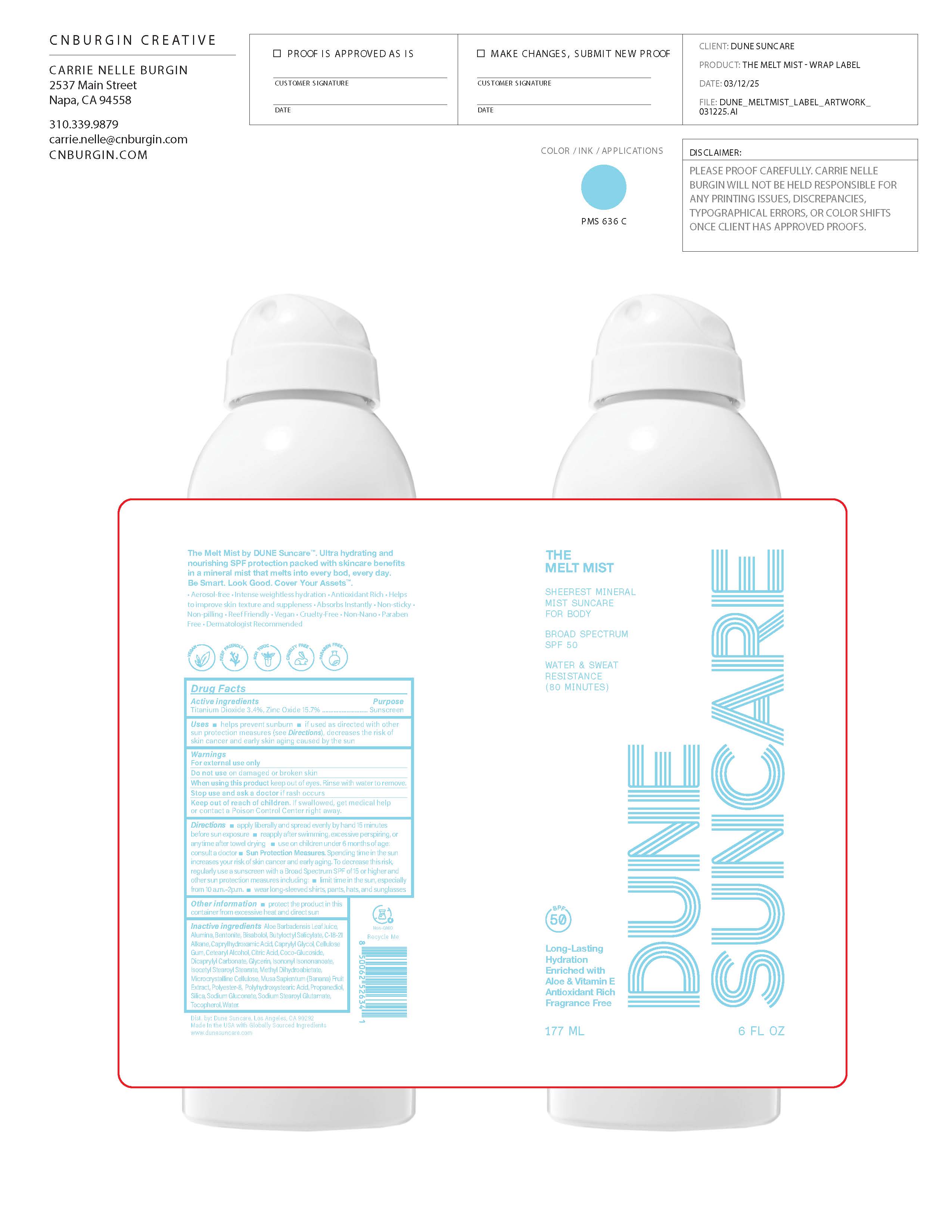 DRUG LABEL: THE MELT MIST
NDC: 82757-205 | Form: SPRAY
Manufacturer: Dune Suncare, Inc.
Category: otc | Type: HUMAN OTC DRUG LABEL
Date: 20251220

ACTIVE INGREDIENTS: TITANIUM DIOXIDE 34 mg/1 mL; ZINC OXIDE 157 mg/1 mL
INACTIVE INGREDIENTS: PROPANEDIOL; BUTYLOCTYL SALICYLATE; SODIUM STEAROYL GLUTAMATE; .ALPHA.-TOCOPHEROL; POLYHYDROXYSTEARIC ACID (2300 MW); SODIUM GLUCONATE; ALUMINA; POLYESTER-8 (1400 MW, CYANODIPHENYLPROPENOYL CAPPED); CAPRYLYL GLYCOL; MUSA ACUMINATA FRUIT; CITRIC ACID; CELLULOSE GUM; ALOE BARBADENSIS LEAF JUICE; CAPRYLHYDROXAMIC ACID; BENTONITE; BISABOLOL; ISONONYL ISONONANOATE; ISOCETYL STEAROYL STEARATE; METHYL DIHYDROABIETATE; WATER; C18-21 ALKANE; GLYCERIN; SILICA, TRIMETHYLSILYL CAPPED; DICAPRYLYL CARBONATE; CETEARYL ALCOHOL; COCO-GLUCOSIDE; MICROCRYSTALLINE CELLULOSE

THE MELT MIST

Active Ingredients

Titanium Dioxide 3.4%

Zinc Oxide 15.7%

Purpose

Sunscreen

Uses

- helps prevent sunburn
- If used as directed with other sun protection measures (see Directions), decreases the risk of skin cancer and early skin aging caused by the sun

Warnings

For external use only

Do not use

on damaged or broken skin

When using this product

keep out of eyes. Rinse with water to remove.

Stop use and ask a doctor

if rash occurs

Keep out of reach of children.

If swallowed, get medical help or contact a Poison Control Center right away.

Directions

- apply liberally and spread evenly by hand 15 minutes before sun exposure
- reapply after swimming, excessive perspiring, or anytime after towel drying
  - use on children under 6 months of age: consult a doctor
- Sun Protection Measures.Spending time in the sun increases your risk of skin cancer and early aging. To decrease this risk, regularly use a sunscreen with Broad Spectrum SPF value of 15 or higher and other sun protection measures including:
- limit time in the sun, especially from 10 a.m.–2 p.m.
- wear long-sleeve shirts, pants, hats, and sunglasses

Other information

- protect the product in this container from excessive heat and direct sun

Inactive ingredients

Aloe Barbadensis Leaf Juice, Alumina, Bentonite, Bisabolol, Butyloctyl Salicylate, C-18-21 Alkane, Caprylhydroxamic Acid, Caprylyl Glycol, Cellulose Gum, Cetearyl Alcohol, Citric Acid, Coco-Glucoside, Dicaprylyl Carbonate, Glycerin, Isononyl Isononanoate, Isocetyl Stearoyl Stearate, Methyl Dihydroabietate, Microcrystalline Cellulose, Musa Sapientum (Banana) Fruit Extract, Polyester-8, Polyhydroxystearic Acid, Propanediol, Silica, Sodium Gluconate, Sodium Stearoyl Glutamate, Tocopherol, Water.

Principal Display Panel

DUNE SUNCARE

THE
MELT MIST

SHEEREST MINERAL

MIST SUNCARE

FOR BODY

BROAD SPECTRUM

SPF 50

WATER & SWEAT

RESISTANCE

(80 MINUTES)

Long-Lasting

Hydration

Enriched with

Aloe & Vitamin E

Antioxidant Rich

Fragrance Free

177 mL

6 FL OZ